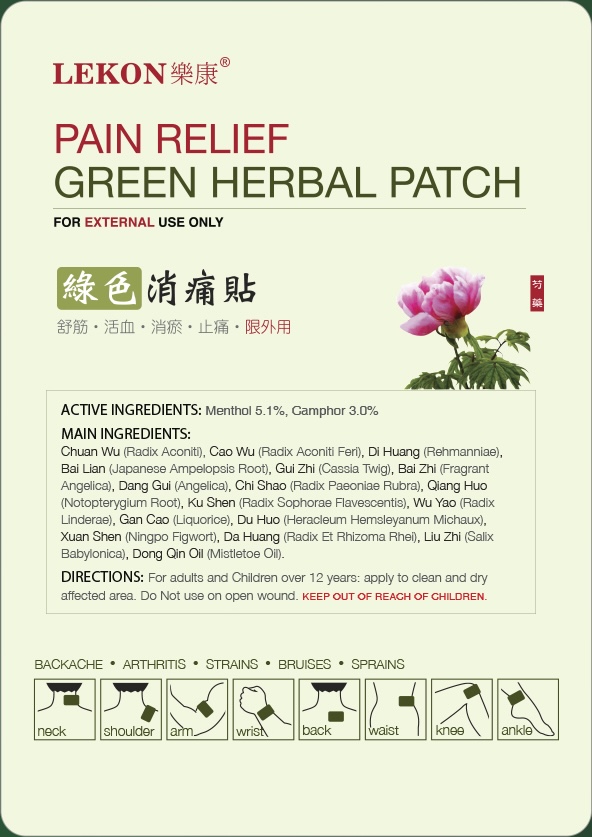 DRUG LABEL: LK Herbal Patch
NDC: 85954-002 | Form: PATCH
Manufacturer: CAI Industries Corp.
Category: otc | Type: HUMAN OTC DRUG LABEL
Date: 20250920

ACTIVE INGREDIENTS: LEVOMENTHOL 5.1 g/1 1
INACTIVE INGREDIENTS: REHMANNIA GLUTINOSA WHOLE

DOSAGE AND ADMINISTRATION

FOR EXTERNAL USE ONLY

ACTIVE INGREDIENTS: Menthol 5.1%, Camphor 3.0%

Do not use on open wound. KEEP OUT OF REACH OF CHILDREN.

INACTIVE INGREDIENT

Chuan Wu (Radix Aconiti), Cao Wu (Radix Aconiti Feri), Di Huang (Rehmanniae), Bai Lian (Japanese Ampelopsis Root), Gui Zhi (Cassia Twig), Bai Zhi (Fragrant Angelica), Dang Gui (Angelica), Chi Shao (Radix Paeoniae Rubra), Qiang Huo (Notopterygium Root), Ku Shen (Radix Sophorae Flavescentis), Wu Yao (Radix Linderae), Gan Cao (Liquorice), Du Huo (Heracleum Hemsleyanum Michaux), Xuan Shen (Ningpo Figwort), Da Huang (Radix Et Rhizoma Rhei), Liu Zhi (Salix Babylonica), Dong Qin Oil (Mistletoe Oil).

INDICATIONS AND USAGE

For adults and children over 12 years: apply to clean and dry affected area.

BACKACHE • ARTHRITIS • STRAINS • BRUISES • SPRAINS

neck, shoulder, arm, wrist, back, waist, knee, ankle

KEEP OUT OF REACH OF CHILDREN.

PURPOSE

PAIN RELIEF
GREEN HERBAL PATCH